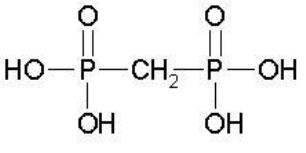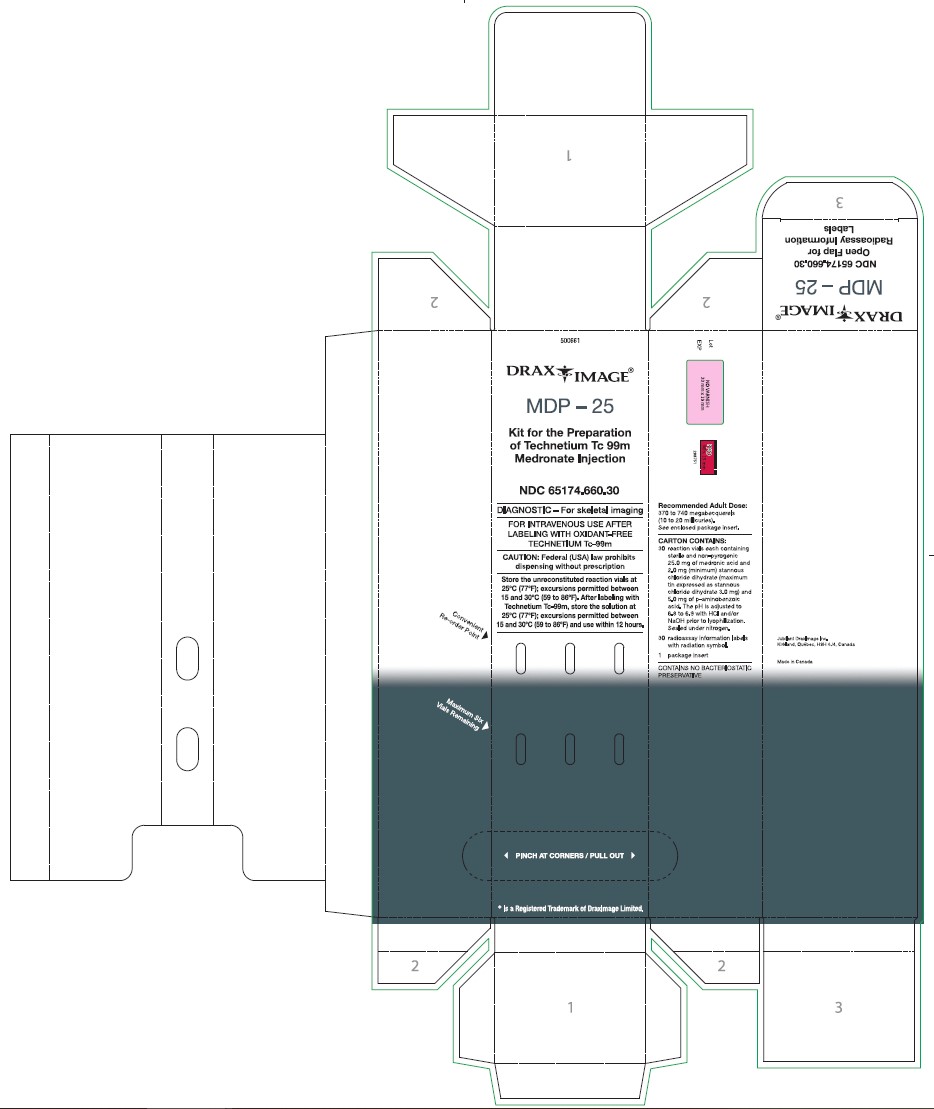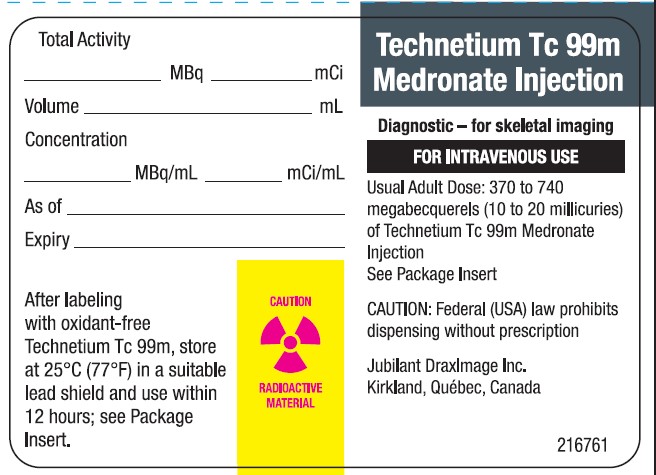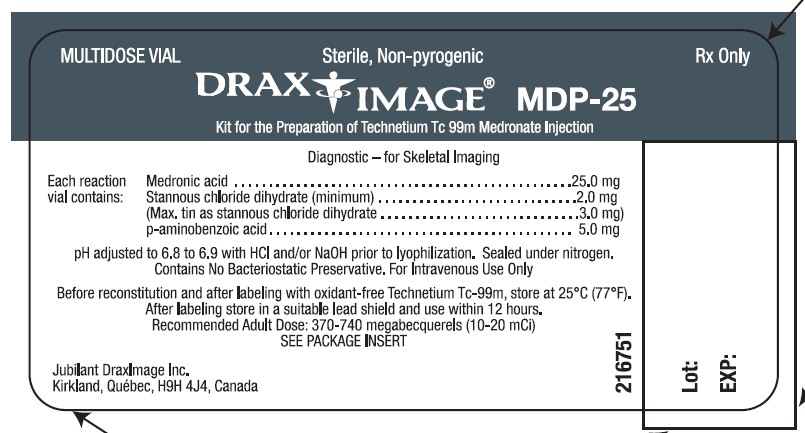 DRUG LABEL: Technetium Tc 99m Medronate 
NDC: 65174-660 | Form: INJECTION, POWDER, FOR SOLUTION
Manufacturer: Jubilant DraxImage Inc., dba Jubilant Radiopharma
Category: prescription | Type: Human Prescription Drug Label
Date: 20250305

ACTIVE INGREDIENTS: MEDRONIC ACID 25 mg/1 1
INACTIVE INGREDIENTS: Stannous Chloride 2.0 mg/1 1; Aminobenzoic Acid 5.0 mg/1 1

DRAXIMAGE® MDP-25 Kit for the Preparation of Technetium Tc 99m Medronate Injection For Intravenous Use DIAGNOSTIC – FOR SKELETAL IMAGING DESCRIPTION

The kit consists of reaction vials which contain the sterile, non-pyrogenic,non-radioactive ingredients necessary to produce Technetium Tc 99m Medronate Injection for diagnostic use by intravenous injection. MDP-25 reaction vials are intended to be used as multidose vials.
Each 10 mL MDP-25 reaction vial contains 25.0 mg medronic acid and not less than 2.0 mg of stannous chloride dihydrate (maximum total tin expressed as stannous chloride dihydrate 3.0 mg) and 5.0 mg of p-aminobenzoic acid in lyophilized form under an atmosphere of nitrogen.
The pH is adjusted to 6.8 to 6.9 with HCI or NaOH prior to lyophilization. The addition of sterile, non-pyrogenic, and oxidant-free sodium pertechnetate Tc-99m sterile solution produces a rapid labeling which is essentially quantitative and which remains stable in vitro throughout the 12-hours life of the preparation. No bacteriostatic preservative is present.
The structural formula of medronic acid is:

PHYSICAL CHARACTERISTICS

Technetium Tc-99m decays by isomeric transition with a physical half-life of 6.02 hours.^1 The principal photon that is useful for detection and imaging studies is listed in Table 1.

Table 1
Principal Radiation Emission Data

Radiation | Mean % / Disintegration | Energy (keV)
Gamma-2 | 89.07 | 140.5

EXTERNAL RADIATION
The specific gamma ray constant for Tc-99m is 0.78 R/mCi-hr at 1 cm. The first half value layer is 0.017 cm of lead. To facilitate control of the radiation exposure from millicurie amounts of this radionuclide, the use of a 0.25 cm thickness of lead will attenuate the radiation emitted by a factor of about 1000. A range of values for the relative attenuation of the radiation emitted by this radionuclide that results from interposition of various thicknesses of lead is shown in Table 2.
Table 2
Radiation Attenuation by Lead Shielding

Shield Thickness (Pb) cm | Coefficient of Attenuation
0.017 0.08 0.16 0.25 0.33 | 0.5 10^-1 10^-2 10^-3 10^-4

To correct for physical decay of this radionuclide, the fractions that remain at selected intervals after the time of calibration are shown in Table 3.
^1Kocher, David C.: “Radioactive Decay Data Tables”, DOE/TIC-11026, 108 (1981)
Table 3
Physical Decay Chart: Tc-99m, half-life 6.02 hours

Hours | Fraction Remaining | Hours | Fraction Remaining
0* 1 2 3 4 5 6 | 1.000 0.891 0.794 0.708 0.631 0.562 0.501 | 7 8 9 10 11 12 | 0.447 0.398 0.355 0.316 0.282 0.251

*Calibration time

CLINICAL PHARMACOLOGY

When injected intravenously, Technetium Tc 99m Medronate is rapidly cleared from the blood; about 50% of the dose is accumulated and retained by the skeleton, while the remaining 50% is excreted in the urine within 24 hours. About 10% of the injected dose remains in the blood at 1 hour post-injection, 5% at 2 hours, and less than 1% remains at 24 hours. The resultant blood clearance curve is tri-exponential with the two fastest components accounting for all but a few percent of the injected dose.
Following intravenous administration of Technetium Tc 99m Medronate, skeletal uptake occurs as a function of blood flow to bone and bone efficiency in extracting the complex. Bone mineral crystals are generally considered to be hydroxyapatite, and the complex appears to have an affinity for the hydroxyapatite crystals in the bone.
The rapid blood clearance provides bone to soft-tissue ratios which favor early imaging. The skeletal uptake is bilaterally symmetrical and is greater in the axial skeleton than in the long bones. Areas of abnormal osteogenesis show altered uptake making it possible to visualize a variety of osseous lesions.

INDICATIONS AND USAGE

MDP-25 (Kit for the Preparation of Technetium Tc 99m Medronate) may be used as a bone imaging agent to delineate areas of altered osteogenesis.

CONTRAINDICATIONS

None known.

WARNINGS

This class of compounds is known to complex cations such as calcium. Particular caution should be used with patients who have, or who may be predisposed to, hypocalcemia (i.e., alkalosis).
The contents of the kit before preparation are not radioactive. However, after the sodium pertechnetate Tc-99m is added, adequate shielding of the final preparation must be maintained.
Preliminary reports indicate impairment of brain images using Sodium Pertechnetate Tc 99m Injection which have been preceded by bone imaging using an agent containing stannous ions. The impairment may result in false-positive or false-negative brain images. It is recommended, where feasible, that brain imaging using Sodium Pertechnetate Tc 99m Injection precede bone imaging procedures. Alternatively, a brain imaging agent such as technetium Tc-99m pentetate may be employed.

The biodistribution of technetium Tc 99m medronate may be altered in the presence of high levels of certain cations (iron, calcium, and aluminum). This may result in reduced uptake of radionuclide in the skeleton and increased extraosseal uptake, which may potentially degrade imaging quality. High levels of these cations may be caused by concomitant medications or medical conditions (e.g., iron overload, hypercalcemia, etc.). Most cases were observed after iron infusion. (See PRECAUTIONS, Drug Interactions.)

PRECAUTIONS

Contents of the reaction vial are intended only for use in the preparation of Technetium Tc 99m Medronate and are NOT to be administered directly to the patient.
To minimize the radiation dose to the bladder, the patient should be encouraged to increase fluid intake and to void as often as possible after the injection of Technetium Tc 99m Medronate, and for 4 to 6 hours after the imaging procedure.
The preparation contains no bacteriostatic preservative.
Both the powdered and reconstituted forms of MDP-25 should be stored at 25°C (77°F); excursions permitted between 15° and 30°C (59° to 86°F). The reconstituted product should be stored in a suitable lead shield. The solution should not be used if it is cloudy.
Optimal imaging results are obtained 1 to 4 hours after administration. The image quality may be adversely affected by obesity, old age and impaired renal function.
General
The components of the kit are sterile and non-pyrogenic. It is essential to follow directions carefully and to adhere to strict aseptic procedures during preparation.
Technetium Tc 99m Medronate as well as other radioactive drugs must be handled with care. Once sodium pertechnetate Tc-99m is added to the vial, appropriate safety measures should be used to minimize external radiation to clinical occupational personnel. Care should also be taken to minimize radiation exposure to patients in a manner consistent with proper patient management.
The technetium Tc-99m labeling reactions involved depend on maintaining the stannous ion in the reduced state. Hence, sodium pertechnetate Tc-99m containing oxidants should not be employed.
Radiopharmaceuticals should be used only by physicians who are qualified by training and experience in the safe use and handling of radionuclides and whose experience and training have been approved by the appropriate government agency authorized to license the use of radionuclides.

Drug Interactions

The biodistribution of technetium Tc 99m medronate may be altered in the presence of high levels of certain cations (iron, calcium, and aluminum). This may result in reduced uptake of radionuclide in the skeleton and increased extraosseal uptake, which may potentially degrade imaging quality. In patients with high levels of these cations caused by concomitant medications, particularly patients receiving iron infusions, consider performing an imaging study with technetium Tc 99m medronate injection once the cation levels have normalized (e.g., after 3 to 5 half-lives of the cation). (See WARNINGS.)

Carcinogenesis, Mutagenesis, Impairment of Fertility
No long term animal studies have been performed to evaluate carcinogenic or mutagenic potential or whether Technetium Tc 99m Medronate affects fertility in males or females.
Pregnancy
Animal reproduction and teratogenicity studies have not been conducted with Technetium Tc 99m Medronate. It is also not known whether Technetium Tc 99m Medronate can cause fetal harm when administered to a pregnant woman or can affect reproductive capacity. There have been no studies in pregnant women. Technetium Tc-99m should be given to a pregnant woman only if clearly needed.
Ideally, examinations using radiopharmaceuticals, especially those elective in nature, of a woman of childbearing capability should be performed during the first few (approximately 10) days following the onset of menses.
Nursing Mothers
Technetium Tc-99m is excreted in human milk during lactation. Therefore, formula feedings should be substituted for breast feedings.
Pediatric Use
Safety and effectiveness in pediatric patients have not been established.

ADVERSE REACTIONS

Several cases of allergic dermatological reactions have been reported in association with the use of Technetium Tc 99m Medronate.
Several reactions have also been reported in association with other radiopharmaceuticals of the diphosphonate class, particularly Technetium Tc 99m Medronate. These are usually hypersensitivity reactions characterized by itching, various skin rashes, hypotension, chills, nausea, fever, and vomiting. One death secondary to cardiac arrhythmia following the administration of Technetium Tc 99m Medronate has been reported. In addition, one case of cardiac arrest in a patient also undergoing pulmonary function testing one and one-half hours after the performance of a bone scan using Technetium Tc 99m Medronate has been reported.

DOSAGE AND ADMINISTRATION

The recommended adult dose, after reconstitution with oxidant-free sodium pertechnetate Tc-99m, is 370 to 740 megabecquerels (10 to 20 millicuries [200 µCi/kg]) by slow intravenous injection over a period of 30 seconds. Optimum scanning time is 1 to 4 hours post-injection.
To minimize the contribution of the bladder content to the image, the patient should void immediately before imaging is started.
The patient dose should be measured by a suitable radioactivity calibration system immediately prior to administration.
Parenteral drug products should be inspected visually for particulate matter and discoloration prior to administration. The solution should not be used if cloudy.
RADIATION DOSIMETRY
The estimated absorbed radiation doses to an average patient (70 kg) from an intravenous injection of a maximum dose of 740 megabecquerels (20 millicuries) of Technetium Tc 99m Medronate are shown in Table 4. The effective half-life was assumed to be the physical half-life for all calculated values.

Table 4
Radiation Doses^2

Tissue | Absorbed Radiation Dose
Tissue | mGy/740 MBq | rads/20 mCi
Total Body Total Bone Red Marrow Kidneys Liver Bladder Wall 2 hr. void 4.8 hr. void Ovaries 2 hr. void 4.8 hr. void Testes 2 hr. void 4.8 hr. void | 1.3 7.0 5.6 8.0 0.6 26.0 62.0 2.4 3.4 1.6 2.2 | 0.13 0.70 0.56 0.80 0.06 2.60 6.20 0.24 0.34 0.16 0.22

^2 Method of calculation: “S” Absorbed Dose per Unit Cumulated Activity for Selected Radionuclides and Organs, MIRD Pamphlet No. 11, 1975

HOW SUPPLIED

MDP-25,
Kit for the Preparation of Technetium Tc 99m Medronate Injection
Product No. 500661 (30 vials)
Available in boxes consisting of 30 reaction vials, each vial containing in lyophilized form, sterile and non-pyrogenic:
Medronic Acid 25.0 mg
Stannous Chloride Dihydrate (minimum) 2.0 mg
(Maximum tin as stannous chloride dihydrate) 3.0 mg
p-Aminobenzoic Acid 5.0 mg
The pH is adjusted to 6.8 to 6.9 with HCI or NaOH prior to lyophilization. The vials are sealed under an atmosphere of nitrogen.
Radioassay information labels with radiation warning symbol and a package insert are supplied in each box.

STORAGE

Store the unreconstituted reaction vials at 25ºC (77ºF); excursions permitted between 15° and 30ºC (59° to 86ºF). After labeling with Technetium Tc-99m, the reconstituted product should be stored at 25ºC (77ºF) in the original vial, and be placed in a suitable lead shield. Excursions permitted between 15° and 30ºC (59° to 86ºF). Discard the reconstituted solution after 12 hours.

DIRECTIONS

NOTE: Use aseptic procedures throughout and take precautions to minimize radiation exposure by use of suitable shielding. Use waterproof gloves during the following preparation procedure.
MDP-25 reaction vials are intended for the preparation of multiple doses of technetium Tc-99m medronate and the entire contents of the vial should not be used as a single dose.
Before reconstituting a vial, it should be inspected for cracks and/or a melted plug or any other indication that the integrity of the vacuum seal has been compromised.
To prepare Technetium Tc 99m Medronate:

1. Remove the central metal disc from a reaction vial and swab the closure with either an alcohol swab or a suitable bacteriostatic agent.
2. Place the reaction vial in a suitable lead vial shield (minimum wall thickness 1/8 inch) which has a fitted lead cap. Obtain 2 to 10 mL of sterile, non-pyrogenic sodium pertechnetate Tc-99m, using a shielded syringe.
  The recommended maximum amount of Technetium Tc-99m to be added to a reaction vial is 37.0 gigabecquerels (1000 mCi). Sufficient sodium pertechnetate is to be used for the reconstitution of a reaction vial to ensure that the dose of medronate administered does not exceed 10 mg. Sodium pertechnetate Tc-99m solutions containing an oxidizing agent are not suitable for use.
3. Using a shielded syringe, add the sodium pertechnetate Tc-99m solution to the reaction vial aseptically.
4. Place the lead cap on the reaction vial shield and agitate the shielded reaction vial until the contents are completely dissolved. The solution must be clear and free of particulate matter before proceeding.
5. Assay the product in a suitable calibrator, record the radioassay information on the label with radiation warning symbol, and apply it to the reaction vial.
6. Withdrawals for administration must be made aseptically using a shielded sterile syringe and needle. Since the reaction vials contain nitrogen to prevent oxidation of the complex, they should not be vented. If repeated withdrawals are made, minimize the replacement of contents with room air.

The following steps should be followed to ensure that each reconstituted of Technetium Tc 99m Medronate contains between 1 and 10 mg of medronic acid.
Where:
Vr = Final volume of in the vial in mL after reconstitution.
C = Concentration of Medronic Acid in mg/mL.
Max. V = Maximum volume to be used for one dose in mL.
Min. V = Minimum volume to be used for one dose in mL.
a) Prior to reconstitution, determine the radioactive concentration of the sodium pertechnetate Tc-99m.
b) Note the volume and activity added to the vial. It should be between 1.85 – 37.0 GBq (50 – 1000 mCi) in 1 to 10 mL.
c) Calculate the concentration (C) of Medronic acid in the vial after reconstitution.
C (mg/mL) = 25 mg ÷ Vr (mL)
d)To ensure that the dose contains a maximum of 10 mg, the following formula should be used to calculate the maximum volume (Max. V) to be dispensed as one dose.
Max. V (mL) = 10 mg ÷ C (mg/mL)
e) To ensure that a minimum dose of 1 mg is dispensed, the following formula should be used to calculate the minimum volume (Min. V) to be dispensed as one dose
Min. V = 1mg ÷ C(mg/mL)

7. The finished preparation should be stored at 25ºC (77ºF);excursions permitted between 15° and 30ºC (59° to 86ºF) when not in use and discarded after 12 hours. It should also be stored during its life in a suitable lead shield.

This reagent kit is approved by the U.S. Nuclear Regulatory Commission for distribution to persons licensed to use by-product material identified in §35.200 to 10 CFR Part 35, to persons who have a similar authorization issued by an Agreement State, and, outside the United States, to persons authorized by the appropriate authority.

NDC 65174-660-30 (30 vials)

Manufactured by:
Jubilant DraxImage Inc.
Kirkland Quebec, H9H 4J4 Canada.
Revised: May 2025